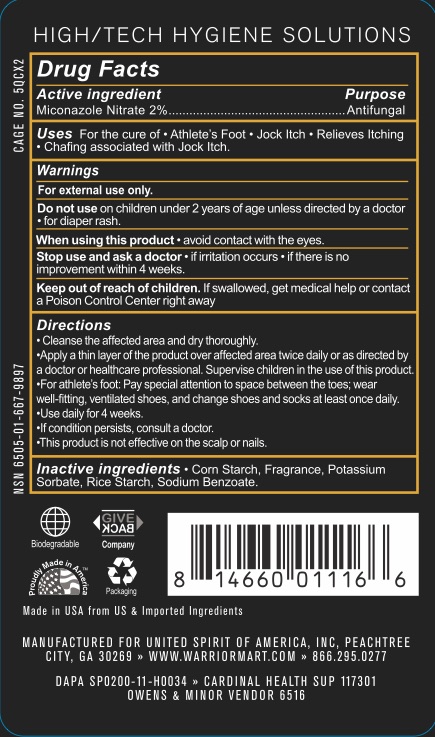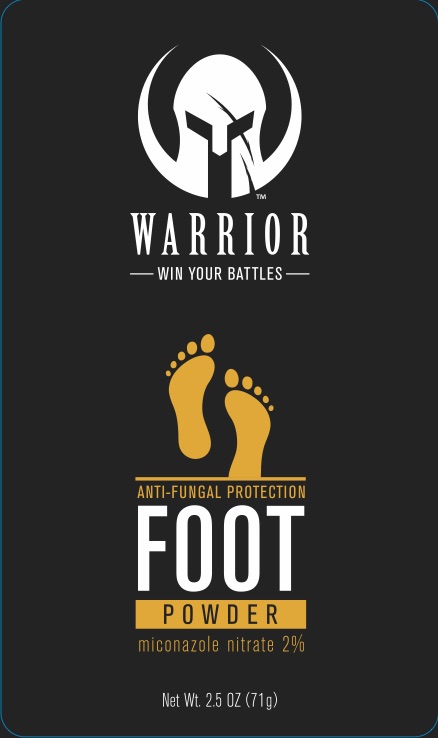 DRUG LABEL: Warrior Antifungal Foot
NDC: 72839-961 | Form: POWDER
Manufacturer: Derma Care Research Labs, LLC
Category: otc | Type: HUMAN OTC DRUG LABEL
Date: 20241220

ACTIVE INGREDIENTS: MICONAZOLE NITRATE 2 g/100 g
INACTIVE INGREDIENTS: SODIUM BENZOATE; STARCH, CORN; POTASSIUM SORBATE; STARCH, RICE

Warrior Antifungal Foot Powder

ACTIVE INGREDIENT

Miconazole Nitrate 2%

PURPOSE

Antifungal

INDICATIONS AND USAGE

For the cure of athlete's foot and jock itch. Relieves itching and chafing associated with jock itch.

WARNINGS

For external use only. Do not use on children under 2 years of age unless directed by a doctor or for diaper rash. When using thisproduct avoid contact with the eyes. Stop use and ask a doctor if irritation occurs or if there is no improvement within 4 weeks.

KEEP OUT OF REACH OF CHILDREN

If swallowed, get medical help or contact a Poison Control Center right away.

DOSAGE AND ADMINISTRATION

Cleanse the affected area and dry thoroughly. Apply a thin layer of the product over the affected area twice daily or as directed by a doctor or healthcare professional. Supervise children in the use of this product.

For athlete's foot: pay special attention to space between the toes; wear well-fitting, ventilated shoes, and change shoes and socks at least once daily. Use daily for 4 weeks.

If the condition persists, consult a doctor.

This product is not effective on the scalp or nails.

INACTIVE INGREDIENT

Corn Starch, Fragrance, Potassium Sorbate, Rice Starch, Sodium Benzoate.